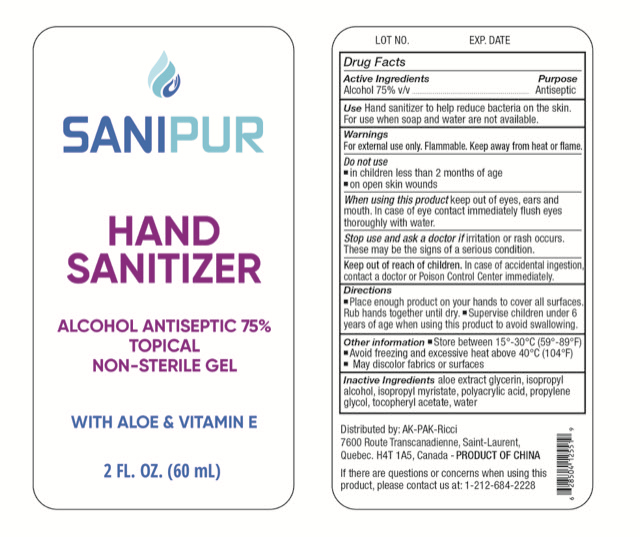 DRUG LABEL: HAND SANITIZER
NDC: 66875-001 | Form: GEL
Manufacturer: SPLENDID KEEN LIMITED
Category: otc | Type: HUMAN OTC DRUG LABEL
Date: 20200611

ACTIVE INGREDIENTS: ALCOHOL 45 mL/60 mL
INACTIVE INGREDIENTS: GLYCERIN; POLYACRYLIC ACID (250000 MW); ALOE; ISOPROPYL MYRISTATE; PROPYLENE GLYCOL; .ALPHA.-TOCOPHEROL ACETATE; ISOPROPYL ALCOHOL; WATER

DOSAGE AND ADMINISTRATION

Store between 15°-30°C (59°-89°F)，Awold freezing and excessive heat above 40°C (104°F)

INACTIVE INGREDIENT

ALOE EXTRACT,GLYCERIN, ISOPROPYL ALCOHOL, ISOPROPYL MYRISTATE, POLYACRYLIC ACID, PROPYLENE GLYCOL, TOCOPHERYL ACETATE, WATER

INDICATIONS AND USAGE

Place enough product on your hands to cover all suraces.Rub hands together until dry.

ACTIVE INGREDIENT

ALCOHOL

keep out of reach of children

PURPOSE

Disinfection
Sterilization
No Rinseing

WARNINGS

For external use only, Flamable. Keep away from heat or flame.